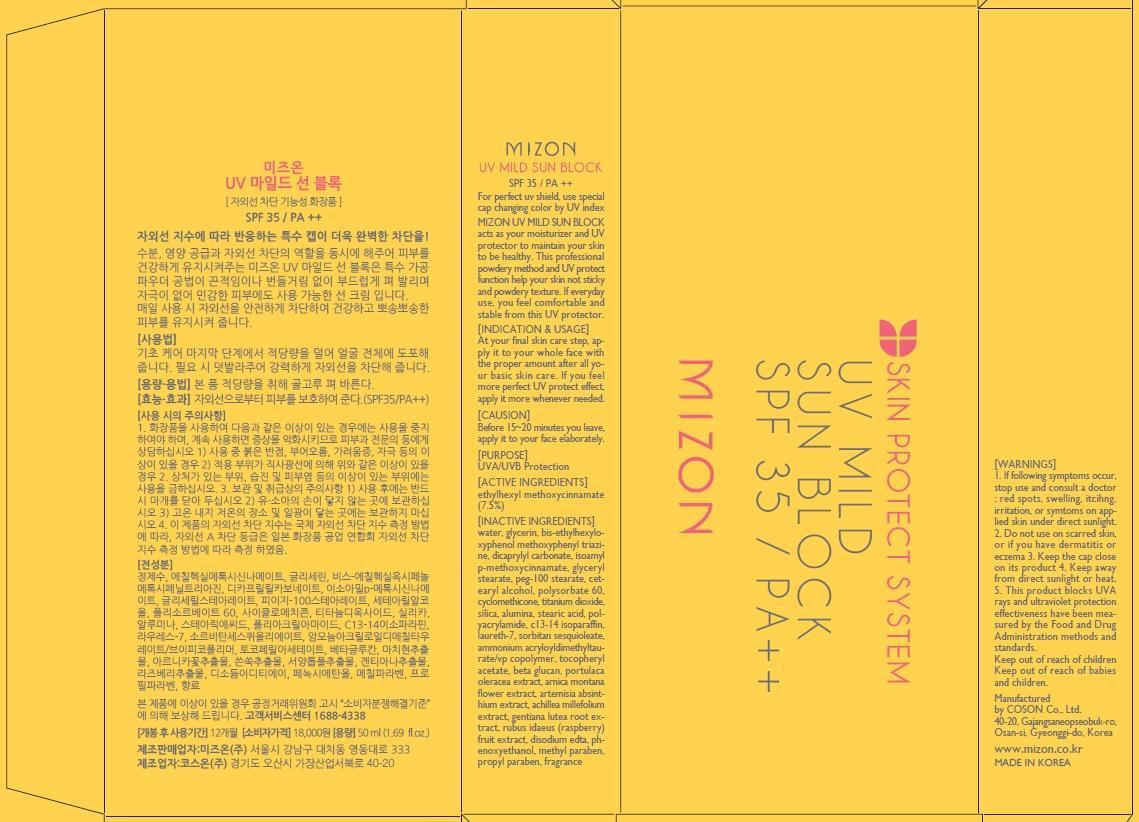 DRUG LABEL: UV MILD SUN BLOCK
NDC: 62171-020 | Form: CREAM
Manufacturer: Coson Co., Ltd.
Category: otc | Type: HUMAN OTC DRUG LABEL
Date: 20140416

ACTIVE INGREDIENTS: OCTINOXATE 3.75 mg/50 mL
INACTIVE INGREDIENTS: WATER; GLYCERIN

ACTIVE INGREDIENT

Active Ingredients: ETHYLHEXYL METHOXYCINNAMATE 7.5%

INACTIVE INGREDIENT

Inactive Ingredients:
WATER, GLYCERIN, BIS-ETHYLHEXYLOXYPHENOL METHOXYPHENYL TRIAZINE, DICAPRYLYL CARBONATE, ISOAMYL p-METHOXYCINNAMATE, GLYCERYL STEARATE, PEG-100 STEARATE, CETEARYL ALCOHOL, POLYSORBATE 60, CYCLOMETHICONE, TITANIUM DIOXIDE, SILICA, ALUMINA, STEARIC ACID, POLYACRYLAMIDE, C13-14 ISOPARAFFIN, LAURETH-7, SORBITAN SESQUIOLEATE, AMMONIUM ACRYLOYLDIMETHYLTAURATE/VP COPOLYMER, TOCOPHERYL ACETATE, BETA GLUCAN, PORTULACA OLERACEA EXTRACT, ARNICA MONTANA FLOWER EXTRACT, ARTEMISIA ABSINTHIUM EXTRACT, ACHILLEA MILLEFOLIUM EXTRACT, GENTIANA LUTEA ROOT EXTRACT, RUBUS IDAEUS (RASPBERRY) FRUIT EXTRACT, DISODIUM EDTA, PHENOXYETHANOL, METHYL PARABEN, PROPYL PARABEN, FRAGRANCE

PURPOSE

Purpose: UVA/UVB Protection

WARNINGS

1. If following symptoms occur, stop use and consult a doctor: red spots, swelling, itcihng, irritation, or symtoms on applied skin under direct sunlight.
2. Do not use on scarred skin, or if you have dermatitis or eczema
3. Keep the cap close on its product.
4. Keep away from direct sunlight or heat.
5. This product blocks UVA rays and ultraviolet protection effectiveness have been measured by the Food and Drug Administration methods and standards.

KEEP OUT OF REACH OF CHILDREN

Keep out of reach of babies and children

INDICATIONS AND USAGE

Indication and Usage:
At your final skin care step, apply it to your whole face with the proper amount after all your basic skin care.
If you feel more perfect UV protect effect, apply it more whenever needed.

DOSAGE AND ADMINISTRATION

Release an appropriate amount and evenly spread over face and body with gentle patting.